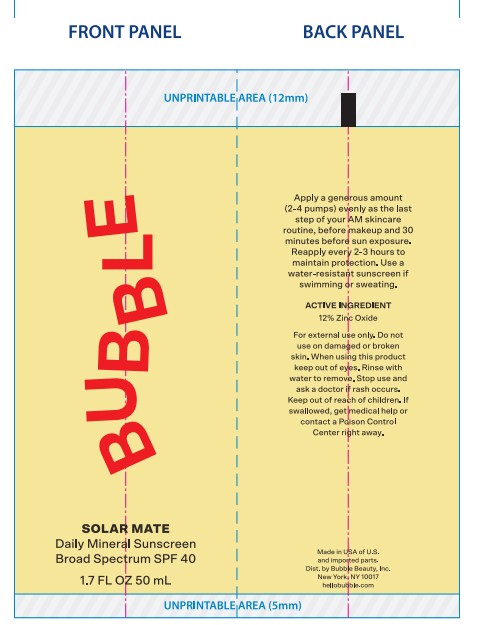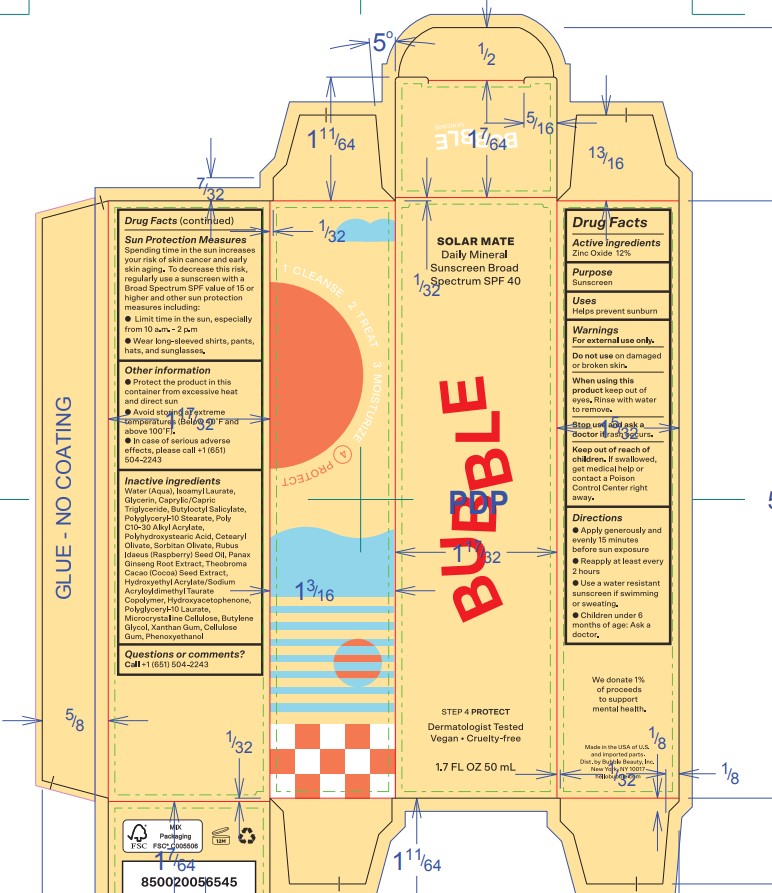 DRUG LABEL: Bubble Solar Mate Daily Mineral Sunscreen SPF 40
NDC: 68577-156 | Form: CREAM
Manufacturer: COSMAX USA, CORPORATION
Category: otc | Type: HUMAN OTC DRUG LABEL
Date: 20241226

ACTIVE INGREDIENTS: ZINC OXIDE 12 mg/100 mg
INACTIVE INGREDIENTS: ISOAMYL LAURATE; GLYCERIN; MEDIUM-CHAIN TRIGLYCERIDES; BUTYLOCTYL SALICYLATE; POLYGLYCERYL-10 STEARATE; BEHENYL ACRYLATE POLYMER; POLYHYDROXYSTEARIC ACID (2300 MW); CETEARYL OLIVATE; SORBITAN OLIVATE; RASPBERRY SEED OIL; ASIAN GINSENG; COCOA; HYDROXYETHYL ACRYLATE/SODIUM ACRYLOYLDIMETHYL TAURATE COPOLYMER (45000 MPA.S AT 1%); WATER; HYDROXYACETOPHENONE; POLYGLYCERYL-10 LAURATE; MICROCRYSTALLINE CELLULOSE; BUTYLENE GLYCOL; XANTHAN GUM; CARBOXYMETHYLCELLULOSE SODIUM; PHENOXYETHANOL

Bubble Solar Mate Daily Mineral Sunscreen SPF 40

Active Ingredients

Zinc Oxide 12%

Purpose

Sunscreen

USES

- helps prevent sunburn

Warnings

For extenal use only

Do not useon damaged or broken skin

WHEN USING

When using this productkeep out of eyes. Rinse with water to remove.

Stop use and ask a doctor ifrash occurs

Keep out of reach of children.If swallowed, get medical help or contact a Poison Control Center right away.

DIRECTIONS

- Apply liberally 15 minutes before sun exposure
- Reapply at least every 2 hours
- Use a water resistant sunscreen if swimming or sweating
- Children under 6 months of age: Ask a doctor

Sun Protection Measures

Spending time in the sun increases your risk of skin cancer and early skin aging. To decrease this risk, regularly use a sunscreen with a Broad Spectrum SPF value of 15 or higher and other sun protection measures including:

- Limit time in the sun, especially from 10 a.m. - 2 p.m.
- Wear long-sleeved shirts, pants, hats, and sunglasses.

OTHER INFORMATION

- Protect the product in this container from excessive heat and direct sun
- Avoid storing at extreme temperatures (Below 40F and above 100F)
- In case of serious adverse effects, please call + (651) 504-2243

INACTIVE INGREDIENT

Inactive ingredientsWater (Aqua), Isoamyl Laurate, Glycerin, Caprylic/Capric Triglyceride, Butyloctyl Salicylate, Polyglyceryl-10 Stearate, Poly C10-30 Alkyl Acrylate, Polyhydroxystearic Acid, Cetearyl Olivate, Sorbitan Olivate, Rubus Idaeus (Raspberry) Seed Oil, Panax Ginseng Root Extract, Theobroma Cacao (Cocoa) Seed Extract, Hydroxyethyl Acrylate/Sodium Acryloyldimethyl Taurate Copolymer, Hydroxyacetophenone, Polyglyceryl-10 Laurate, Microcrystalline Cellulose, Butylene Glycol, Xanthan Gum, Cellulose Gum, Phenoxyethanol.

QUESTIONS or COMMENTS

Call+1 (651) 504-2243

Primary Package(Inner)

Outer Package (Secondary)